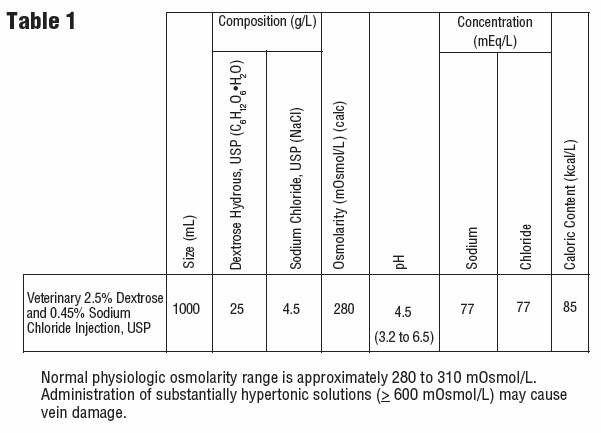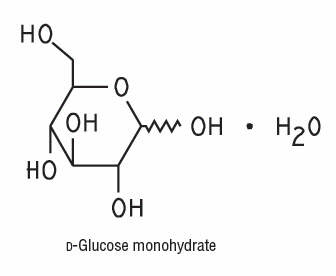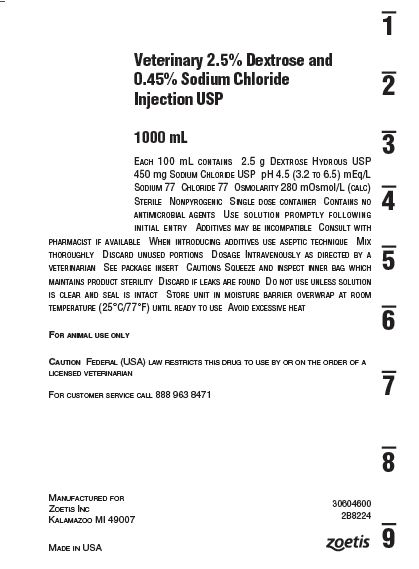 DRUG LABEL: Veterinary Dextrose and Sodium Chloride
NDC: 54771-4933 | Form: INJECTION, SOLUTION
Manufacturer: Zoetis Inc.
Category: animal | Type: PRESCRIPTION ANIMAL DRUG LABEL
Date: 20160809

ACTIVE INGREDIENTS: DEXTROSE MONOHYDRATE 2.5 g/100 mL; SODIUM CHLORIDE 450 mg/100 mL

Veterinary 2.5% Dextrose and 0.45% Sodium Chloride Injection, USP

For Animal Use Only

Description

2.5% Dextrose and 0.45% Sodium Chloride Injection, USP is a sterile, nonpyrogenic solution for fluid and electrolyte replenishment and caloric supply in single dose containers for intravenous administration. It contains no antimicrobial agents. Discard unused portion. Composition, osmolarity, pH, concentration and caloric content are shown in Table 1.

The plastic container is fabricated from a specially formulated polyvinyl chloride. The amount of water that can permeate from inside the container into the overwrap is insufficient to affect the solution significantly. Solutions in contact with the plastic container can leach out certain of its chemical components in very small amounts within the expiration period, e.g., di-2-ethylhexyl phthalate (DEHP), up to 5 parts per million. However, the safety of the plastic has been confirmed in tests in animals according to USP biological tests for plastic containers as well as by tissue culture toxicity studies.

Clinical Pharmacology

2.5% Dextrose and 0.45% Sodium Chloride Injection, USP has value as a source of water, electrolytes, and calories. It is capable of inducing diuresis depending on the clinical condition of the patient.

Indications and Usage

2.5% Dextrose and 0.45% Sodium Chloride Injection, USP is indicated as a source of water, electrolytes, and calories.

Contraindications

Solutions containing dextrose may be contraindicated in patients with known allergy to corn or corn products.

Warnings

2.5% Dextrose and 0.45% Sodium Chloride Injection, USP should be used with great care, if at all, in patients with congestive heart failure, severe renal insufficiency, and in clinical states in which there exists edema with sodium retention.

2.5% Dextrose injections with low electrolyte concentrations should not be administered simultaneously with blood through the same administration set because of the possibility of pseudoagglutination or hemolysis.

The intravenous administration of 2.5% Dextrose and 0.45% Sodium Chloride Injection, USP can cause fluid and/or solute overloading resulting in dilution of serum electrolyte concentrations, overhydration, congested states, or pulmonary edema. The risk of dilutional states is inversely proportional to the electrolyte concentrations of the injections. The risk of solute overload causing congested states with peripheral and pulmonary edema is directly proportional to the electrolyte concentrations of the injections.

Excessive administration of 2.5% Dextrose and 0.45% Sodium Chloride Injection, USP may result in significant hypokalemia.

In patients with diminished renal function, administration of 2.5% Dextrose and 0.45% Sodium Chloride Injection, USP may result in sodium retention.

Adverse Reactions

Reactions which may occur because of the solution or the technique of administration include febrile response, infection at the site of injection, venous thrombosis or phlebitis extending from the site of injection, extravasation and hypervolemia.

If an adverse reaction does occur, discontinue the infusion, evaluate the patient, institute appropriate therapeutic countermeasures and save the remainder of the fluid for examination if deemed necessary.

Precautions

Clinical evaluation and periodic laboratory determinations are necessary to monitor changes in fluid balance, electrolyte concentrations, and acid base balance during prolonged parenteral therapy or whenever the condition of the patient warrants such evaluation.

Caution must be exercised in the administration of 2.5% Dextrose and 0.45% Sodium Chloride Injection, USP to patients receiving corticosteroids or corticotropin.

2.5% Dextrose and 0.45% Sodium Chloride Injection, USP should be used with caution in patients with overt or subclinical diabetes mellitus.

Do not administer unless solution is clear and seal is intact.

Dosage and Administration

As directed by a veterinarian. Dosage is dependent upon the age, weight, and clinical condition of the patient as well as laboratory determinations.

Parenteral drug products should be inspected visually for particulate matter and discoloration prior to administration whenever solution and container permit.

All injections in plastic containers are intended for intravenous administration using sterile equipment.

Additives may be incompatible. Complete information is not available.

Those additives known to be incompatible should not be used. Consult with veterinarian, if available. If, in the informed judgment of the veterinarian, it is deemed advisable to introduce additives, use aseptic technique. Mix thoroughly when additives have been introduced.
Do not store solutions containing additives.

OverDosage

In an event of overhydration or solute overload, re-evaluate the patient and institute appropriate corrective measures. See Warnings , Precautions and Adverse Events .

How Supplied

2.5% Dextrose and 0.45% Sodium Chloride Injection, USP in plastic container is supplied as follows:

Size (mL) Code
1000 2B8224

Exposure of pharmaceutical products to heat should be minimized.
Avoid excessive heat. It is recommended the product be stored at room temperature (25°C/77°F); brief exposure up to 40°C/104°F does not adversely affect the product.

Directions for use of plastic container

To Open

Tear overwrap down side at slit and remove solution container. Some opacity of the plastic due to moisture absorption during the sterilization process may be observed. This is normal and does not affect the solution quality or safety. The opacity will diminish gradually. Check for minute leaks by squeezing inner bag firmly. If leaks are found, discard solution as sterility may be impaired. If supplemental medication is desired, follow directions below.

Preparation for Administration
1. Suspend container from eyelet support.
2. Remove protector from outlet port at bottom of container.
3. Attach administration set. Refer to complete directions accompanying set.

To Add Medication
WARNING: Additives may be incompatible.
To add medication before solution administration
1. Prepare medication site.
2. Using syringe with 19 to 22 gauge needle, puncture resealable medication port and inject.
3. Mix solution and medication thoroughly. For high density medication such as potassium chloride, squeeze ports while ports are upright and mix thoroughly.

To add medication during solution administration
1. Close clamp on the set.
2. Prepare medication site.
3. Using syringe with 19 to 22 gauge needle, puncture resealable medication port and inject.
4. Remove container from IV pole and/or turn to an upright position.
5. Evacuate both ports by squeezing them while container is in the upright position.
6. Mix solution and medication thoroughly.
7. Return container to in use position and continue administration.

CAUTION: Federal law restricts this drug to use by or on the order of a licensed veterinarian.

Manufactured for:

Zoetis Inc.

Kalamazoo, MI 49007

For customer service call (888) 963-8471

Printed in USA

07-19-74-711

30603500

Rev. October 2015

Principal Display Panel

Veterinary 2.5% Dextrose and

0.45% Sodium Chloride

Injection USP

1000 mL

Label for Veterinary Dextrose and Sodium Chloride